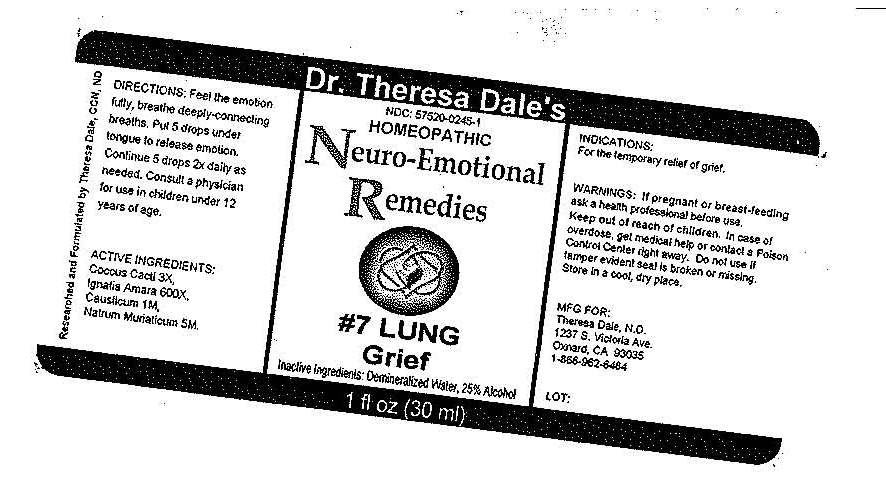 DRUG LABEL: 7 Lung
NDC: 57520-0245 | Form: LIQUID
Manufacturer: Apotheca Company
Category: homeopathic | Type: HUMAN OTC DRUG LABEL
Date: 20100810

ACTIVE INGREDIENTS: CAUSTICUM 1 [hp_M]/1 mL; SODIUM CHLORIDE 5 [hp_M]/1 mL; STRYCHNOS IGNATII SEED 600 [hp_X]/1 mL; PROTORTONIA CACTI 3 [hp_X]/1 mL
INACTIVE INGREDIENTS: WATER; ALCOHOL

#7 Lung

ACTIVE INGREDIENT

ACTIVE INGREDIENTS: Causticum 1M, Natrum muriaticum 5M, Ingatia amara 600X, Coccus cacti 3X.

PURPOSE

INDICATIONS: For the temporary relief of grief.

WARNINGS

WARNINGS: If pregnant or breast-feeding, ask a health professional before use.

Keep out of reach of children. In case of overdose, get medical help or contact a Poison Control Center right away.

Do not use if tamper evident seal is broken or missing. Store in a cool, dry place.

DOSAGE AND ADMINISTRATION

DIRECTIONS: Feel the emotion fully, breathe deeply-connecting breaths. Put 5 drops under tongue to release emotion. Continue 5 drops 2x daily as needed. Consult a physician for use in children under 12 years of age.

INACTIVE INGREDIENTS: Demineralized water, 25% Alcohol.

QUESTIONS

MFG FOR:

Theresa Dale, N.D.

1237 S. Victoria Ave.

Oxnard, CA 93035

1-856-962-6484

PACKAGE LABEL

Dr. Theresa Dale's

HOMEOPATHIC

Neuro-Emotional Remedies

#7 LUNG

Grief

1 fl oz (30 ml)